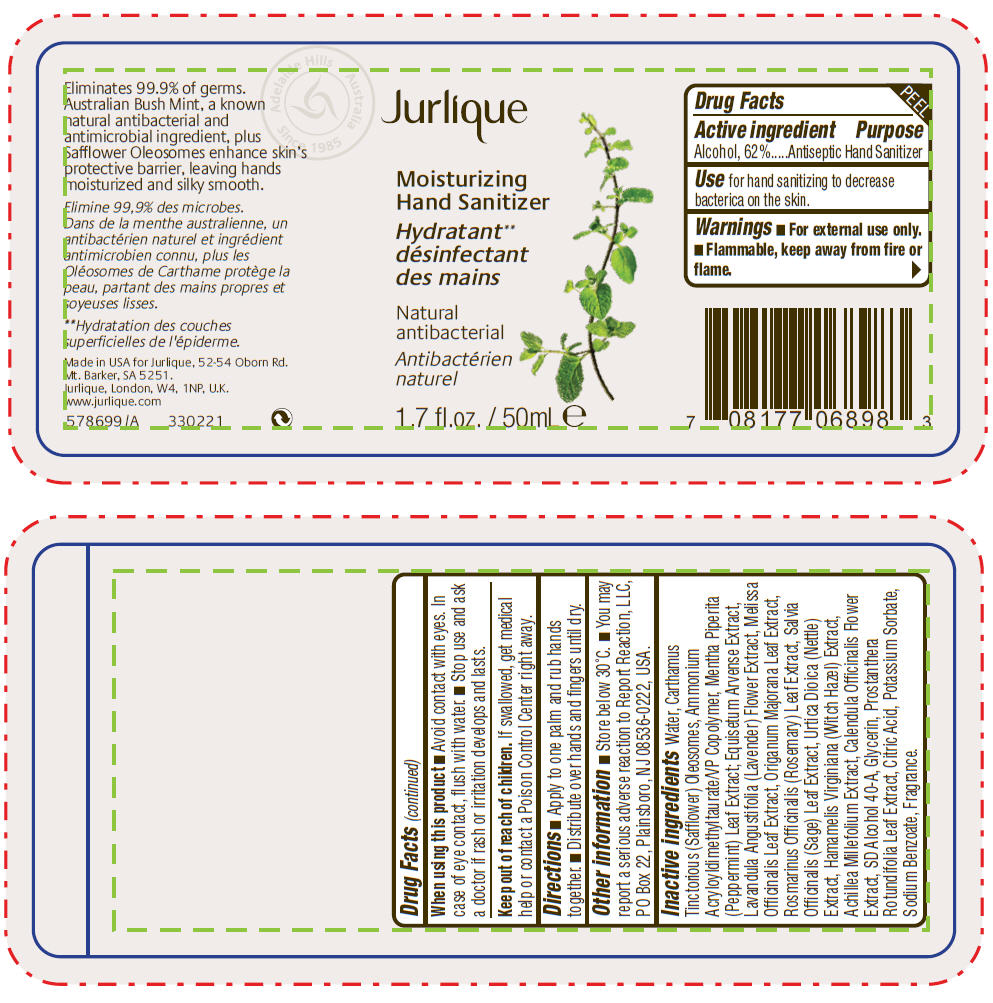 DRUG LABEL: Jurlique Moisturizing Hand Sanitizer 
NDC: 68105-003 | Form: LOTION
Manufacturer: Jurlique International Pty. Ltd.
Category: otc | Type: HUMAN OTC DRUG LABEL
Date: 20110112

ACTIVE INGREDIENTS: ALCOHOL 613.8 mg/1 mL
INACTIVE INGREDIENTS: WATER; SAFFLOWER; EQUISETUM ARVENSE BRANCH; LAVANDULA ANGUSTIFOLIA FLOWER; HAMAMELIS VIRGINIANA LEAF; ACHILLEA MILLEFOLIUM; CALENDULA OFFICINALIS FLOWER; MENTHA PIPERITA LEAF; MELISSA OFFICINALIS LEAF; SWEET MARJORAM OIL; ROSEMARY; SAGE; URTICA DIOICA LEAF; GLYCERIN; CITRIC ACID MONOHYDRATE; POTASSIUM SORBATE; SODIUM BENZOATE

Jurlique
Moisturizing
Hand Sanitizer

Drug Facts

Active ingredient

Alcohol, 62 %

Purpose

Antiseptic Hand Sanitizer

Use

for hand sanitizing to decrease bacteria on the skin

Warnings

- For external use only
- Flammable, keep away from fire or flame

When using this product

- Avoid contact with eyes. In case of eye contact, flush with water
- Stop use and ask a doctor if rash or irritation develops and lasts

Keep out of reach of children. If swallowed, get medical help or contact a Poison Control Center right away

Directions

- Apply to one palm and rub hands together
- Distribute over hands and fingers until dry

Other information

- Store below 30°C
- You may report a serious adverse reaction to Report Reaction, LLC PO Box 22, Plainsboro, NJ 08536-022

Inactive ingredients

Water, Carthamus Tinctorious (Safflower) Oleosomes, Ammonium Acryloyldimethyltaurate/VP Copolymer, Mentha Piperita (Peppermint) Leaf Extract, Equisetum Arvense Extract, Lavandula Angustifolia (Lavender) Flower Extract, Melissa Officinalis Leaf Extract, Origanum Majorana Leaf Extract, Rosmarinus Officinalis (Rosemary) Leaf Extract, Salvia Officinalis (Sage) Leaf Extract, Urtica Dioica (Nettle) Extract, Hamamelis Virginiana (Witch Hazel) Extract, Achillea Millefolium Extract, Calendula Officinalis Flower Extract, SD Alcohol 40-A, Glycerin, Prostanthera Rotundifolia Leaf Extract, Citric Acid, Potassium Sorbate, Sodium Benzoate, Fragrance

Made in USA for Jurlique,
52-54 Oborn Rd., Mt. Barker, SA 5251.
Jurlique, London, W4 1NP U.K.
www.jurlique.com

PRINCIPAL DISPLAY PANEL - 50mL Bottle Label

Jurlique

Moisturizing
Hand Sanitizer

Natural
antibacterial

1.7 fl.oz. / 50mL e